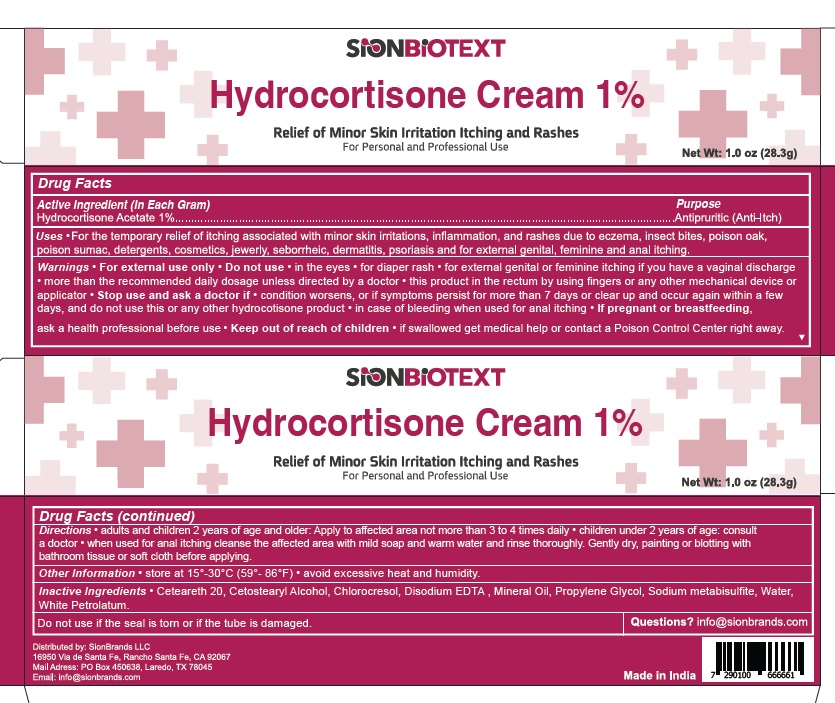 DRUG LABEL: SionBiotext Hydrocortisone
NDC: 68786-001 | Form: CREAM
Manufacturer: Sion Biotext Medical Ltd
Category: otc | Type: HUMAN OTC DRUG LABEL
Date: 20250513

ACTIVE INGREDIENTS: HYDROCORTISONE ACETATE 0.1 g/1 g
INACTIVE INGREDIENTS: CETEARETH-20; CETOSTEARYL ALCOHOL; CHLOROCRESOL; EDETATE SODIUM; MINERAL OIL; PROPYLENE GLYCOL; SODIUM METABISULFITE; WATER; WHITE PETROLATUM

Active Ingredient (In Each Gram)

Hydrocortisone Acetate 1%

Purpose

Antipruritic (Anti-Itch)

Uses

For the temporary relief of itching associated with minor skin irritations, inflammation, and rashes due to:

- Eczema
- insect bites
- poison oak
- poison sumac
- detergents
- cosmetics
- jewelry
- seborrheic
- dermatitis
- psoriasis
- for external genital
- feminine
- anal itching

Warnings

For external use only

Do not use

- in the eyes
- for diaper rash
- for external genital or feminine itching if you have a vaginal discharge
- more than the recommend daily dosage unless directed by a doctor
- this product in the rectum by using fingers or any other mechanical device or applicator
- if the seal is torn or if the tube is damaged

Stop use and ask a doctor if

- condition worsens, or if symptoms persists for more than 7 days or clears up and occurs again within a few days,and do not use this or any other hydrocortisone product
- in case of bleeding when used for anal itching

If pregnant or breastfeeding

ask a health professional before use

Keep out of reach of children

If swallowed get medical help or contact a Posion Control Center right away

Directions

- adults and children 2 years of age and older. Apply to affected area not more than 3 to 4 times daily.
- children under 2 of age: consult a doctor
- when used for anal itching cleanse the affected area with mild soap and warm water and rinse thoroughly. Gently dry, painting or blotting with bathroom tissue or soft cloth before applying.

Other Information

- Store at 15°-30°C (59°-86°F)
- avoid excessive heat and humidity

Inactive Ingredients

Ceteareth 20, Cetostearyl Alcohol, Chlorocresol, Disodium EDTA, Mineral Oil, Propylene Glycol, Sodium metabisulfite, Water, White Petrolatum

Questions

info@sionbrands.com

Unclassified Section

Distributed by: SIonBrands LLC

16950 Via de Santa Fe, Rancho Santa Fe, CA, 92067

Mail Address: PO Box 450638, Laredo, TX, 78045

Email: info@sionbrands.com

Made in India

Principal Display Panel

NDC 68786-001-28

SIONBIOTEXT

Hydrocortisone Cream 1%

Relief of Minor Skin Irritiation Itching and Rashes

For Personal and Professional Use

Net Wt: 1.0 oz (28.3g)